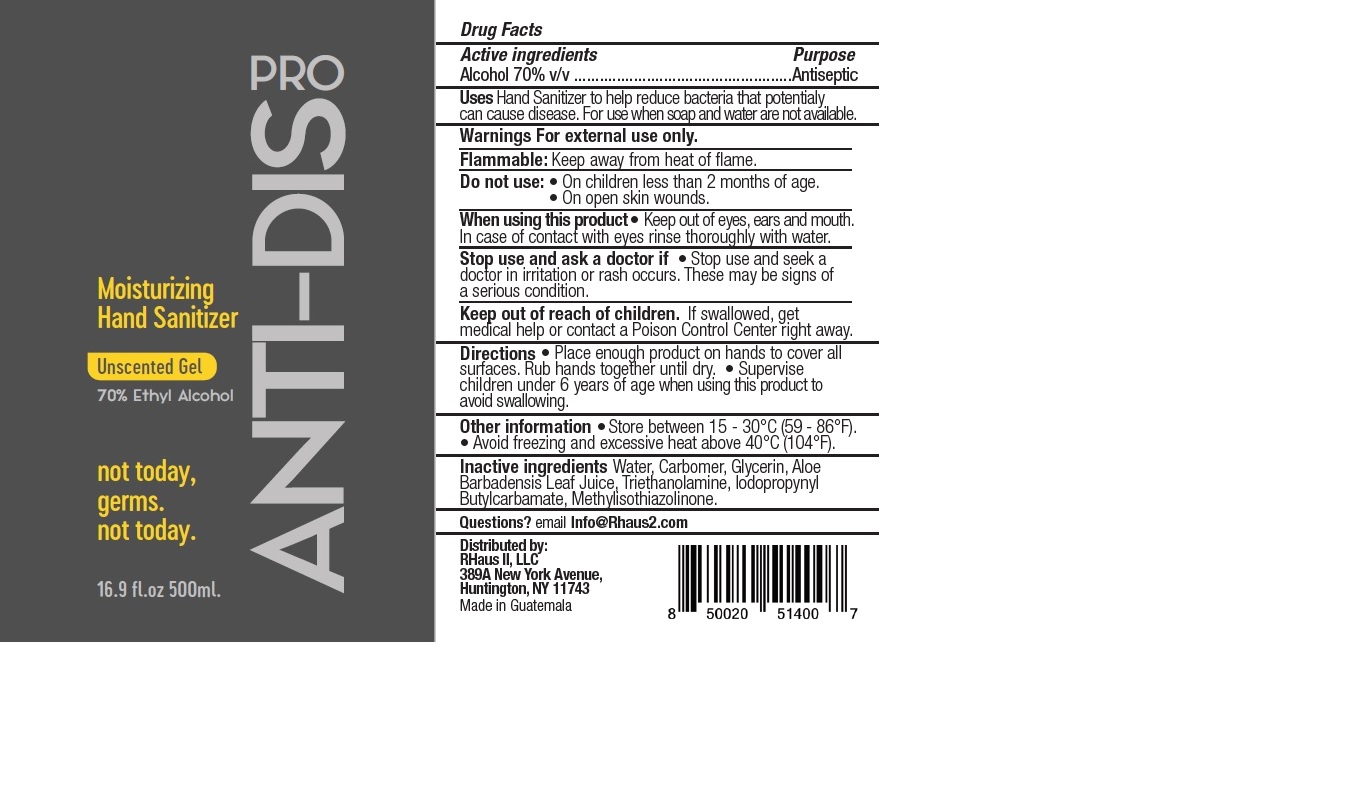 DRUG LABEL: MOISTURIZING HAND SANITIZER
NDC: 79181-001 | Form: GEL
Manufacturer: RHaus II, LLC
Category: otc | Type: HUMAN OTC DRUG LABEL
Date: 20200623

ACTIVE INGREDIENTS: ALCOHOL 70 mL/100 mL
INACTIVE INGREDIENTS: GLYCERIN; CARBOMER HOMOPOLYMER, UNSPECIFIED TYPE; METHYLISOTHIAZOLINONE; IODOPROPYNYL BUTYLCARBAMATE; TROLAMINE; WATER; ALOE VERA LEAF

RHaus Moisturizing Hand Sanitizer

Active ingredients

Alcohol 70% v/v

Purpose

Antiseptic

Uses

Hand Sanitizer to help reduce bacteria that potentially can cause disease. For use when soap and water are not available.

Warnings

For external use only. Flammable. Keep away from fire or flame.

Do not use

- On children less than 2 months of age.
- On open skin wounds.

When using this product

- Keep out of eyes, ears and mouth. In case of contact with eyes rinse thoroughly with water.

Stop use and ask a doctor if

- Stop use and seek a doctor if irritation or rash occurs. These may be signs of a serious condition.

Keep out of reach of children.

If swallowed, get medical help or contact a Poison Control Center right away.

Directions

- Place enough product on hands to cover all surfaces. Rub hands together until dry.
- Supervise children under 6 years of age when using this product to avoid swallowing.

Other information

- Store between 15-30C (59-86F).
- Avoid freezing and excessive heat above 40C (104F)

Inactive ingredients

Water, Carbomer, Glycerin, Aloe Barbadensis Leaf Juice, Triethanolamine, Iodopropynyl Butylcarbamate, Methylisothiazolinone.

Questions?

email Info@Rhaus2.com

Company Information

Distributed By:

RHaus II, LLC

389A New York Avenue

Huntington, NY 11743

Made in Guatemala

Product Packaging

ANTI-DIS PRO

Moisturizing Hand Sanitizer

Unscented Gel

70% Ethyl Alcohol

not today,

germs.

not today.

16.9 fl.oz 500ml